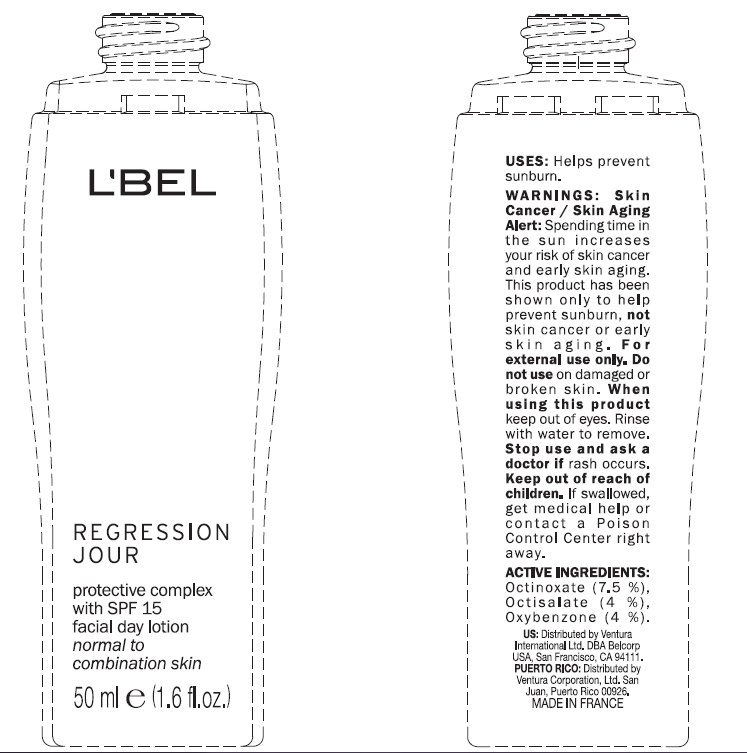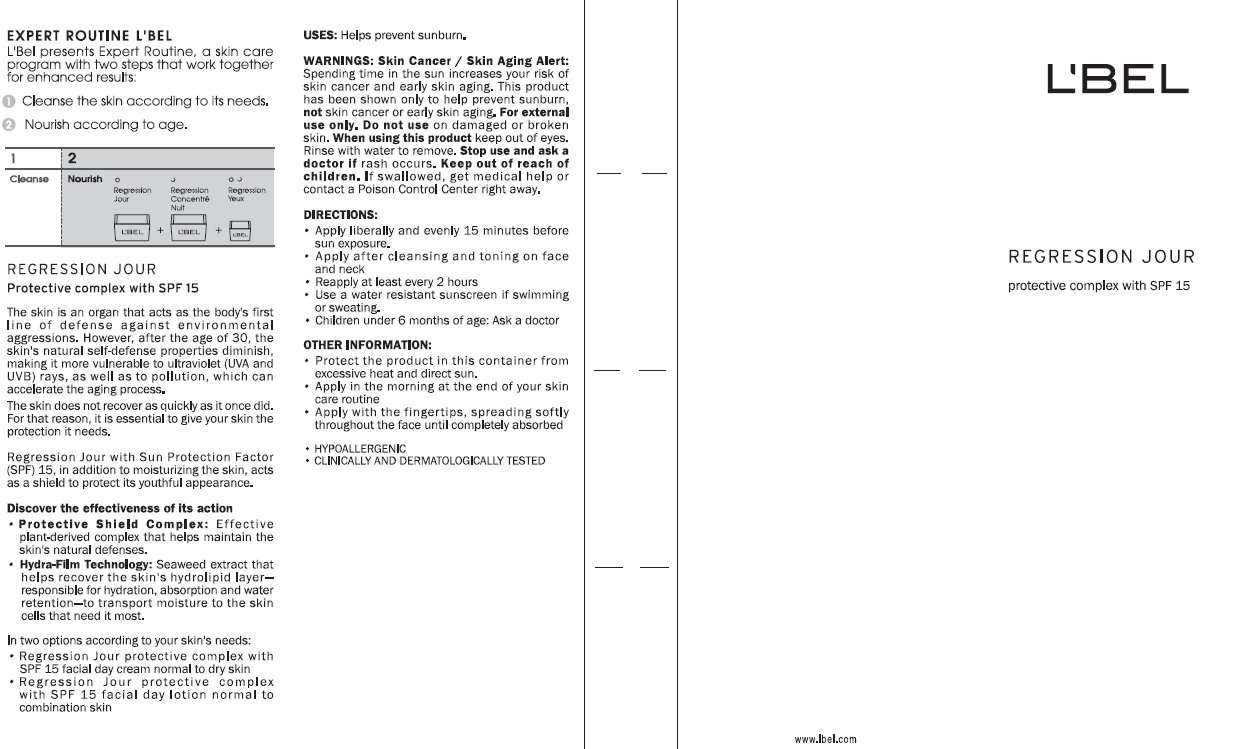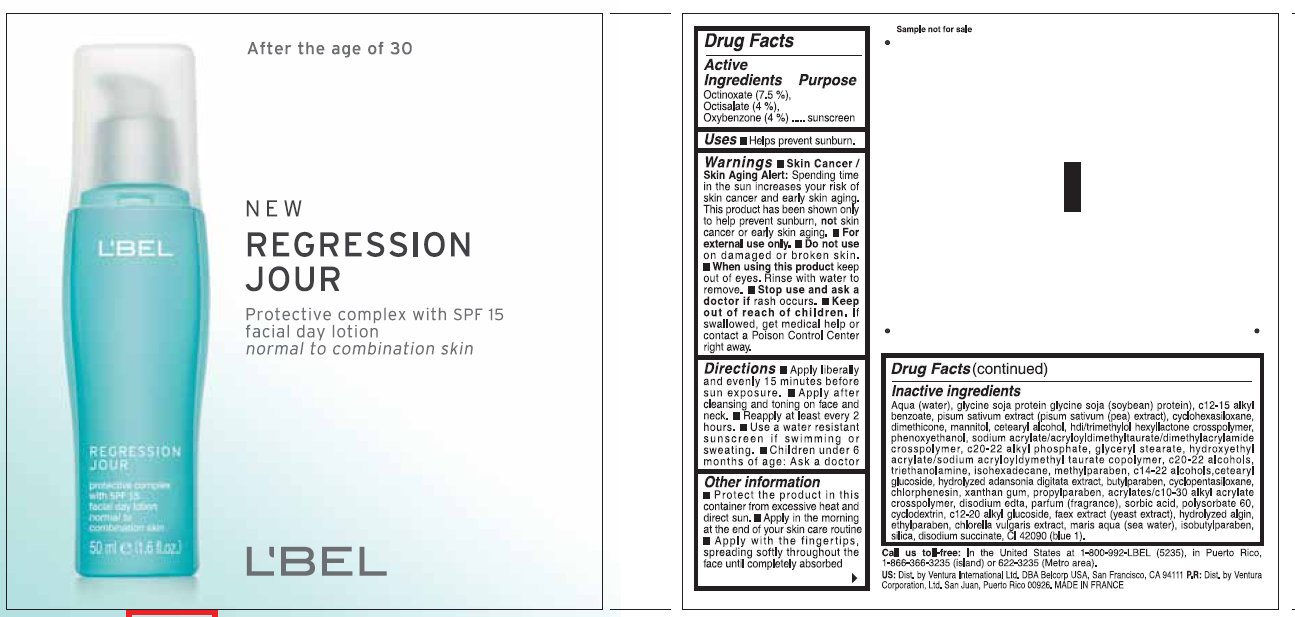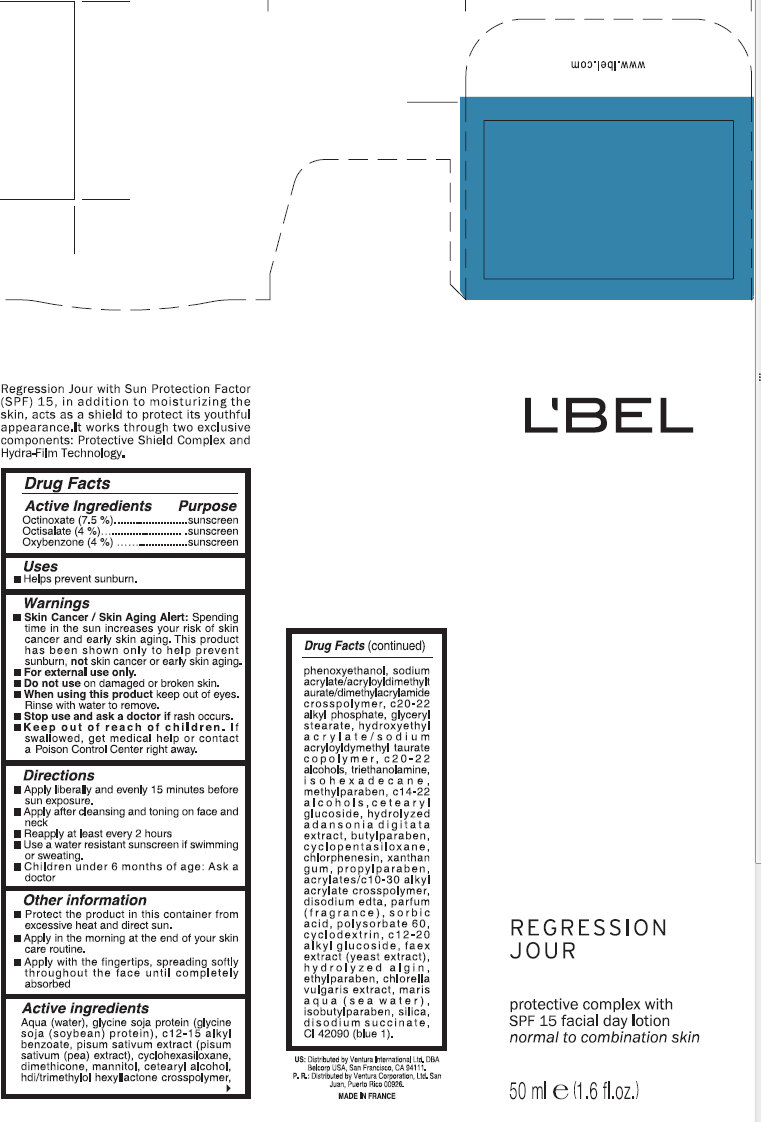 DRUG LABEL: LBEL REGRESSION JOUR Protective Complex With SPF 15 Facial Day Normal to Combination Skin
NDC: 43455-0003 | Form: LOTION
Manufacturer: Ventura International, LTD
Category: otc | Type: HUMAN OTC DRUG LABEL
Date: 20120328

ACTIVE INGREDIENTS: OCTINOXATE 7.5 mL/100 mL; OCTISALATE 4 mL/100 mL; OXYBENZONE 4 mL/100 mL
INACTIVE INGREDIENTS: WATER; SOY PROTEIN; ALKYL (C12-15) BENZOATE; PEA; CYCLOMETHICONE 6; DIMETHICONE; MANNITOL; CETOSTEARYL ALCOHOL; PHENOXYETHANOL; SODIUM ACRYLATE/SODIUM ACRYLOYLDIMETHYLTAURATE COPOLYMER (4000000 MW); C20-22 ALKYL PHOSPHATE; GLYCERYL MONOSTEARATE; 2-HYDROXYETHYL ACRYLATE; C20-22 ALCOHOLS; TROLAMINE; ISOHEXADECANE; METHYLPARABEN; C14-22 ALCOHOLS; CETEARYL GLUCOSIDE; BUTYLPARABEN; CYCLOMETHICONE 5; CHLORPHENESIN; XANTHAN GUM; PROPYLPARABEN; CARBOMER INTERPOLYMER TYPE A (55000 MPA.S); EDETATE DISODIUM; SORBIC ACID; POLYSORBATE 60; C12-20 ALKYL GLUCOSIDE; YEAST; ETHYLPARABEN; CHLORELLA VULGARIS; ISOBUTYLPARABEN; SILICON DIOXIDE; SODIUM SUCCINATE ANHYDROUS; D&C BLUE NO. 4

L'BEL REGRESSION JOUR Protective Complex With SPF 15 Facial Day Lotion Normal to Combination Skin

Active Ingredients

Octinoxate (7.5%)
Octisalate (4%)
Oxybenzone (4%)

Uses

- Helps prevent sunburn.

Warnings

- Skin Cancer / Skin Aging Alert: Spending time in the sun increases your risk of skin cancer and early skin aging. This product has been shown only to help prevent sunburn, not skin cancer or early skin aging.

- For external use only.

Do not use

on damaged or broken skin.

When using this product

keep out of eyes. Rinse with water to remove.

Stop use and ask a doctor if

rash occurs.

Keep out of reach of children.

If swallowed, get medical help or contact a Poison Control Center right away.

Directions

- Apply liberally and evenly 15 minutes before sun exposure.
- Apply after cleansing and toning on face and neck
- Reapply at least every 2 hours.
- Use a water resistant sunscreen if swimming or sweating.
- Children under 6 months of age: Ask a doctor.

Other information

- Protect the product in this container from excessive heat and direct sun.
- Apply in the morning at the end of your skin care routine.
- Apply with the fingertips, spreading softly throughout the face until completely absorbed

Inactive Ingredients

AQUA (WATER), GLYCINE SOJA PROTEIN (GLYCINE SOJA (SOYBEAN) PROTEIN), C12-15 ALKYL BENZOATE, PISUM SATIVUM EXTRACT (PISUM SATIVUM (PEA) EXTRACT), CYCLOHEXASILOXANE, DIMETHICONE, MANNITOL, CETEARYL ALCOHOL, HDI/TRIMETHYLOL HEXYLLACTONE CROSSPOLYMER, PHENOXYETHANOL, SODIUM ACRYLATE/ACRYLOYLDIMETHYLTAURATE/DIMETHYLACRYLAMIDE CROSSPOLYMER, C20-22 ALKYL PHOSPHATE, GLYCERYL STEARATE, HYDROXYETHYL ACRYLATE/SODIUM ACRYLOYLDYMETHYL TAURATE COPOLYMER, C20-22 ALCOHOLS, TRIETHANOLAMINE, ISOHEXADECANE, METHYLPARABEN, C14-22 ALCOHOLS,CETEARYL GLUCOSIDE, HYDROLYZED ADANSONIA DIGITATA EXTRACT, BUTYLPARABEN, CYCLOPENTASILOXANE, CHLORPHENESIN, XANTHAN GUM, PROPYLPARABEN, ACRYLATES/C10-30 ALKYL ACRYLATE CROSSPOLYMER, DISODIUM EDTA, PARFUM (FRAGRANCE), SORBIC ACID, POLYSORBATE 60, CYCLODEXTRIN, C12-20 ALKYL GLUCOSIDE, FAEX EXTRACT (YEAST EXTRACT), HYDROLYZED ALGIN, ETHYLPARABEN, CHLORELLA VULGARIS EXTRACT, MARIS AQUA (SEA WATER), ISOBUTYLPARABEN, SILICA, DISODIUM SUCCINATE, CI 42090 (BLUE 1)

Purpose

Sunscreen

Call us toll-free: In the United States at 1-800-992-LBEL (5235), in Puerto Rico, 1-866-366-3235 (Metro area). US: Dis. by Ventura International Ltd.

US: Dis. by Ventura International Ltd. DBA Belcorp USA, San Francisco, CA 94111 P.R.: Dist. by Ventura Corporation Ltd., San Juan, Puerto Rico 00926. MADE IN FRANCE

EXPERT ROUTINE L'BEL

L'Bel presents Expert Routine, a skin care program with two steps that work together for enhanced results:

1. Cleanse the skin according to its needs
2. Noursih according to age

PROGRESSION JOUR
Protective complex with SPF 15
The skin is an organ that acts as the body's first line of defense against environmental aggressions. However, after the age of 30, the skin's natural self-defense properties diminish, making it more vulnerable to ultraviolet (UVA and UVB) rays, as well as to pollution, which can accelerate the aging process.
The skin does not recover as quickly as it once did. For that reason, it is essential to give your skin the protection it needs.
Regression Jour with Sun Protection Factor (SPF) 15, in addition to moisturizing the skin, acts as a shield to protect its youthful appearance.
Discover the effectiveness of its action

- Protective Shield Complex: Effective plant-derived complex that helps maintain the skin's natural defenses.
- Hydra-Film Technology: Seaweed extract that helps recover the skin's hydrolipid layer - responsible for hydration, absorption and water retention - to transport moisture to the skin cells that need it most.

In two options according to your skin's needs:

- Regression Jour protective complex with SPF 15 facial day cream normal to dry skin.
- Regression Jour protective complex with SPF 15 facial day cream normal to combination skin.

USES: Helps prevent sunburn.
WARNINGS: Skin Cancer / Skin Aging Alert: Spending time in the sun increases your risk of skin cancer and early skin aging. This product has been shown only to help prevent sunburn not skin cancer or early skin aging. For external use only. Do not use on damaged or broken skin. When using this product keep out of eyes. Rinse with water to remove. Stop use and ask a doctor if rash occurs. Keep out of reach of children. If swallowed, get medical help or contact a Poison Control Center right away.
DIRECTIONS:

- Apply liberally and evenly 15 minutes before sun exposure.
- Apply after cleansing and toning on face and neck
- Reapply at least every 2 hours
- Use a water resistant sunscreen if swimming or sweating.
- Children under 6 months of age: Ask a doctor

OTHER INFORMATION:

- Protect the product in this container from excessive heat and direct sun.
- Apply in the morning at the end of your skin care routine
- Apply with fingertips, spreading softly throughout the face until completely absorbed
- HYPOALLERGENIC
- CLINICALLY AND DERMATOLOGICALLY TESTED

PACKAGE LABEL

After the age of 30

NEW REGRESSION JOUR Protective complex with SPF 15 facial day lotion normal to combination skin 50 ml e (1.6 fl. oz.) L'BEL